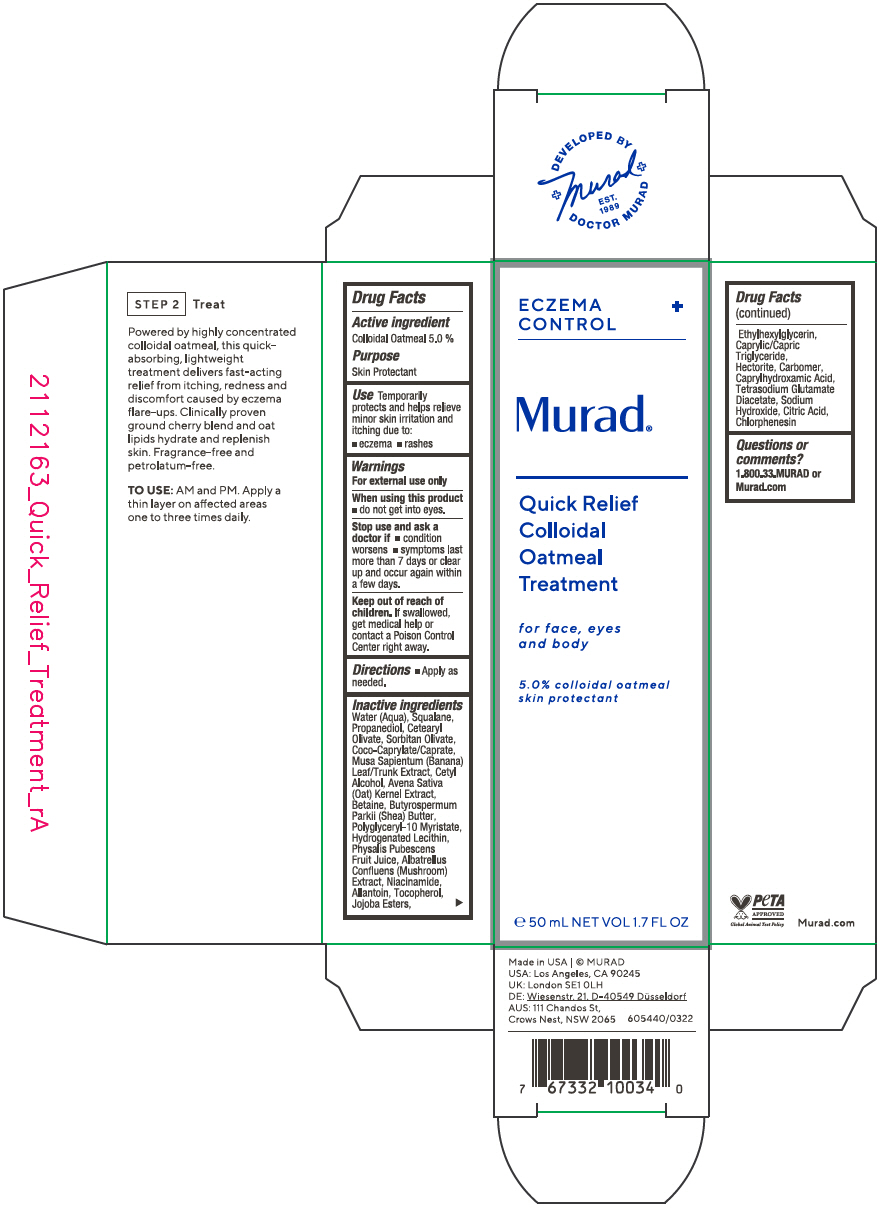 DRUG LABEL: Quick Relief Colloidal Oatmeal Treatment 
NDC: 70381-123 | Form: SOLUTION
Manufacturer: Murad, LLC
Category: otc | Type: HUMAN OTC DRUG LABEL
Date: 20220617

ACTIVE INGREDIENTS: OATMEAL 5 g/100 mL
INACTIVE INGREDIENTS: WATER; SQUALANE; PROPANEDIOL; CETEARYL OLIVATE; SORBITAN OLIVATE; COCOYL CAPRYLOCAPRATE; CETYL ALCOHOL; OAT; BETAINE; SHEA BUTTER; POLYGLYCERYL-10 MYRISTATE; HYDROGENATED SOYBEAN LECITHIN; PHYSALIS PUBESCENS FRUIT JUICE; ALBATRELLUS CONFLUENS FRUITING BODY; NIACINAMIDE; ALLANTOIN; TOCOPHEROL; HYDROGENATED JOJOBA OIL, RANDOMIZED; ETHYLHEXYLGLYCERIN; MEDIUM-CHAIN TRIGLYCERIDES; HECTORITE; CARBOMER HOMOPOLYMER, UNSPECIFIED TYPE; CAPRYLHYDROXAMIC ACID; TETRASODIUM GLUTAMATE DIACETATE; SODIUM HYDROXIDE; CITRIC ACID MONOHYDRATE; CHLORPHENESIN; MUSA X PARADISIACA LEAF

Quick Relief Colloidal Oatmeal Treatment
for face, eyes and body

Drug Facts

Active ingredient

Colloidal Oatmeal 5.0 %

Purpose

Skin Protectant

Use

Temporarily protects and helps relieve minor skin irritation and itching due to:

- eczema
- rashes

Warnings

For external use only

When using this product

- do not get into eyes.

Stop use and ask a doctor if

- condition worsens
- symptoms last more than 7 days or clear up and occur again within a few days.

Keep out of reach of children. If swallowed, get medical help or contact a Poison Control Center right away.

Directions

- Apply as needed.

Inactive ingredients

Water (Aqua), Squalane, Propanediol, Cetearyl Olivate, Sorbitan Olivate, Coco-Caprylate/Caprate, Musa Sapientum (Banana) Leaf/Trunk Extract, Cetyl Alcohol, Avena Sativa (Oat) Kernel Extract, Betaine, Butyrospermum Parkii (Shea) Butter, Polyglyceryl-10 Myristate, Hydrogenated Lecithin, Physalis Pubescens Fruit Juice, Albatrellus Confluens (Mushroom) Extract, Niacinamide, Allantoin, Tocopherol, Jojoba Esters, Ethylhexylglycerin, Caprylic/Capric Triglyceride, Hectorite, Carbomer, Caprylhydroxamic Acid, Tetrasodium Glutamate Diacetate, Sodium Hydroxide, Citric Acid, Chlorphenesin

Questions or comments?

1.800.33.MURAD or Murad.com

PRINCIPAL DISPLAY PANEL - 50 mL Tube Carton

ECZEMA
CONTROL
+

Murad®

Quick Relief
Colloidal
Oatmeal
Treatment

for face, eyes
and body

5.0% colloidal oatmeal
skin protectant

℮ 50 mL NET VOL 1.7 FL OZ